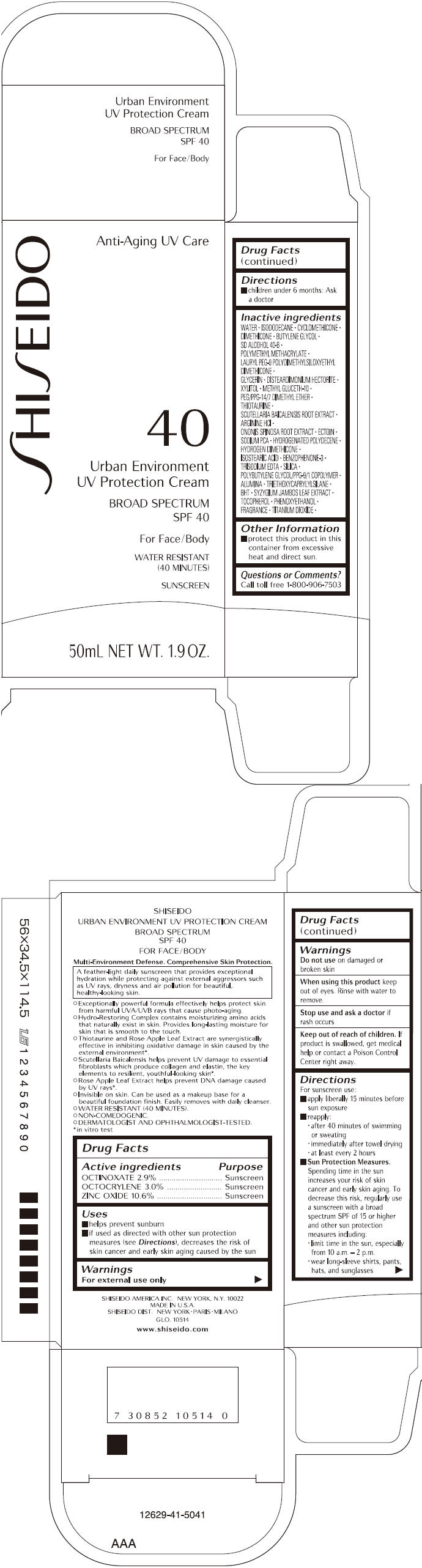 DRUG LABEL: SHISEIDO URBAN ENVIRONMENT UV PROTECTION
NDC: 52686-271 | Form: CREAM
Manufacturer: SHISEIDO AMERICA INC.
Category: otc | Type: HUMAN OTC DRUG LABEL
Date: 20181213

ACTIVE INGREDIENTS: OCTINOXATE 1583 mg/54.6 g; OCTOCRYLENE 1638 mg/54.6 g; ZINC OXIDE 5788 mg/54.6 g
INACTIVE INGREDIENTS: WATER; ISODODECANE; CYCLOMETHICONE; DIMETHICONE; BUTYLENE GLYCOL; GLYCERIN; XYLITOL; METHYL GLUCETH-10; THIOTAURINE; SCUTELLARIA BAICALENSIS ROOT; ARGININE HYDROCHLORIDE; ONONIS CAMPESTRIS ROOT; ECTOINE; SODIUM PYRROLIDONE CARBOXYLATE; HYDROGENATED POLYDECENE (550 MW); ISOSTEARIC ACID; OXYBENZONE; EDETATE TRISODIUM; SILICON DIOXIDE; ALUMINUM OXIDE; TRIETHOXYCAPRYLYLSILANE; BUTYLATED HYDROXYTOLUENE; SYZYGIUM JAMBOS LEAF; .ALPHA.-TOCOPHEROL; PHENOXYETHANOL; TITANIUM DIOXIDE

SHISEIDO URBAN ENVIRONMENT UV PROTECTION
CREAM

Drug Facts

ACTIVE INGREDIENT

ACTIVE INGREDIENTS: | Purpose
OCTINOXATE 2.9% | Sunscreen
OCTOCRYLENE 3.0% | Sunscreen
ZINC OXIDE 10.6% | Sunscreen

Uses

- helps prevent sunburn
- if used as directed with other sun protection measures (see Directions), decreases the risk of skin cancer and early skin aging caused by the sun

Warnings

For external use only

Do not use on damaged or broken skin

When using this product keep out of eyes. Rinse with water to remove.

Stop use and ask a doctor if rash occurs

Keep out of reach of children. If product is swallowed, get medical help or contact a Poison Control Center right away.

Directions

For sunscreen use:

- apply liberally 15 minutes before sun exposure
- reapply:
  - after 40 minutes of swimming or sweating
  - immediately after towel drying
  - at least every 2 hours
- Sun Protection Measures. Spending time in the sun increases your risk of skin cancer and early skin aging. To decrease this risk, regularly use a sunscreen with a broad spectrum SPF of 15 or higher and other sun protection measures including:
  - limit time in the sun, especially from 10 a.m. – 2 p.m.
  - wear long-sleeve shirts, pants, hats, and sunglasses
- children under 6 months: Ask a doctor

Inactive Ingredients

WATER, ISODODECANE, CYCLOMETHICONE, DIMETHICONE, BUTYLENE GLYCOL, SD ALCOHOL 40-B, POLYMETHYL METHACRYLATE, LAURYL PEG-9 POLYDIMETHYLSILOXYETHYL DIMETHICONE, GLYCERIN, DISTEARDIMONIUM HECTORITE, XYLITOL, METHYL GLUCETH-10, PEG/PPG-14/7 DIMETHYL ETHER, THIOTAURINE, SCUTELLARIA BAICALENSIS ROOT EXTRACT, ARGININE HCl, ONONIS SPINOSA ROOT EXTRACT, ECTOIN, SODIUM PCA, HYDROGENATED POLYDECENE, HYDROGEN DIMETHICONE, ISOSTEARIC ACID, BENZOPHENONE-3, TRISODIUM EDTA, SILICA, POLYBUTYLENE GLYCOL/PPG-9/1 COPOLYMER, ALUMINA, TRIETHOXYCAPRYLYLSILANE, BHT, SYZYGIUM JAMBOS LEAF EXTRACT, TOCOPHEROL, PHENOXYETHANOL, FRAGRANCE, TITANIUM DIOXIDE,

Other information

- protect this product in this container from excessive heat and direct sun.

Questions or comments?

Call toll free 1-800-906-7503

SHISEIDO DIST. NEW YORK • PARIS • MILANO

PRINCIPAL DISPLAY PANEL - 50mL Tube Carton

SHI SEIDO

Anti-Aging UV Care

40

Urban Enviroment
UV Protection Cream

BROAD SPECTRUM
SPF 40

For Face/Body

WATER RESISTANT
(40 MINUTES)

SUNSCREEN

50mL NET WT. 1.9 OZ.